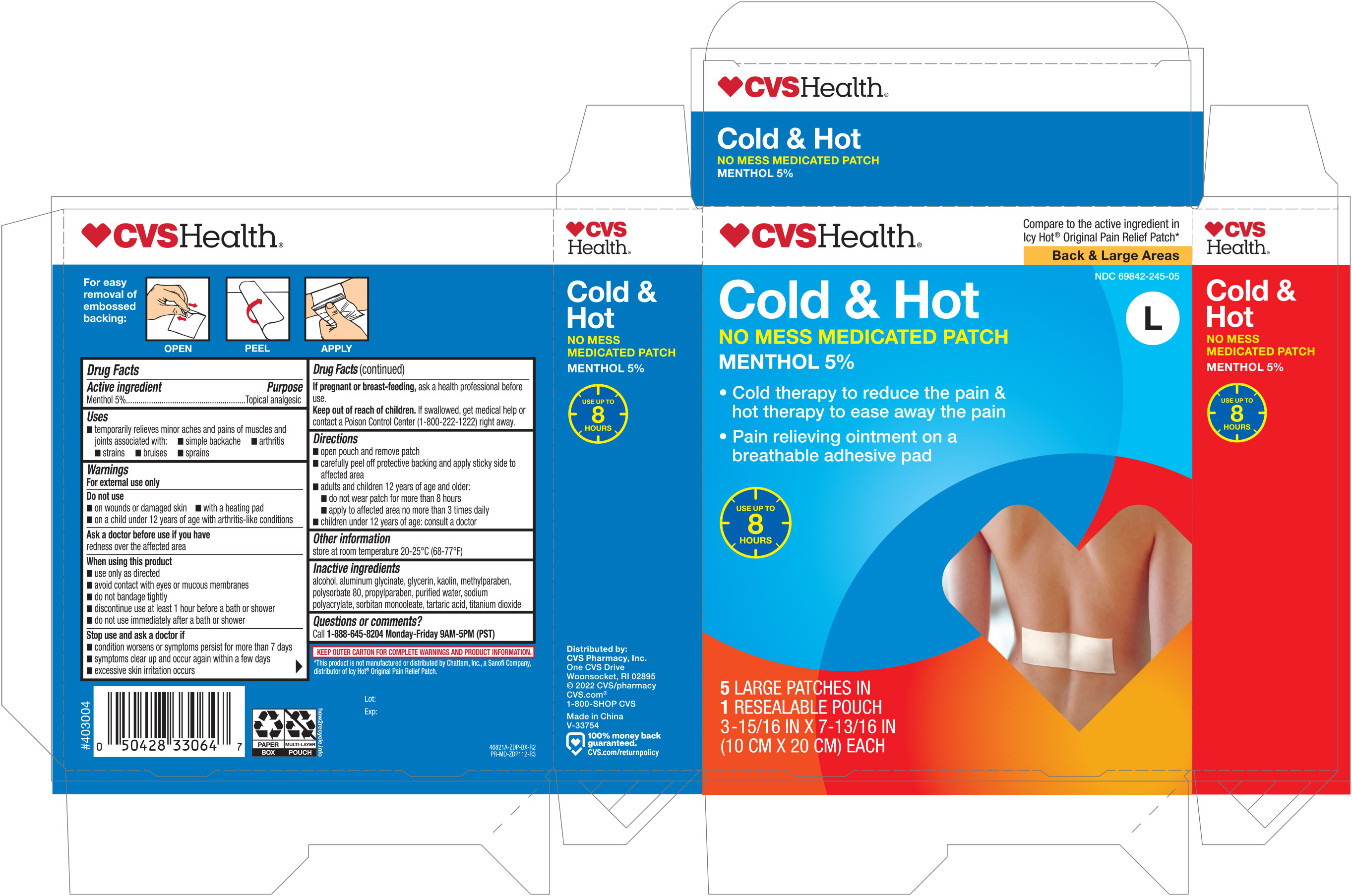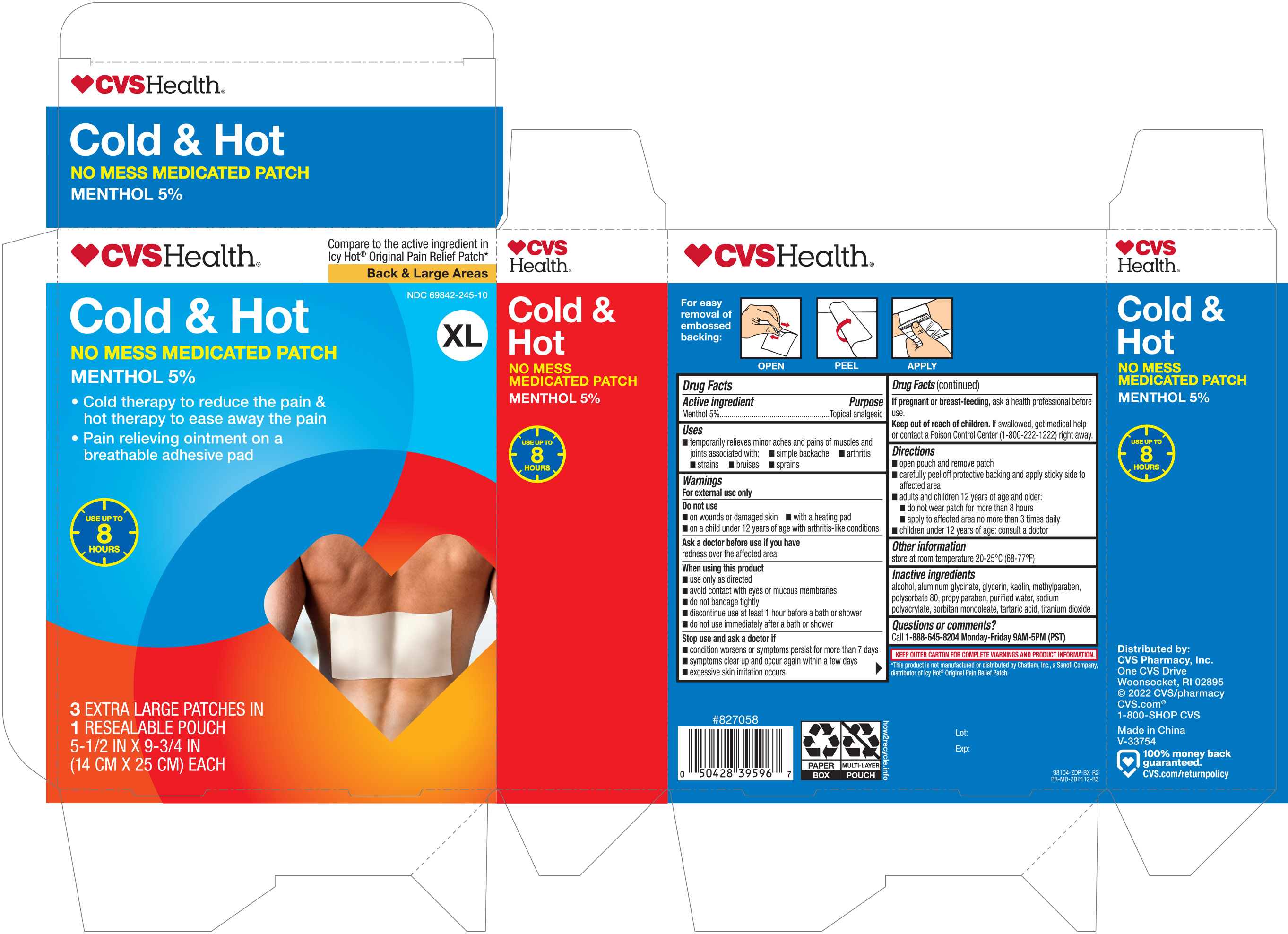 DRUG LABEL: CVS Cold and Hot
NDC: 69842-245 | Form: PATCH
Manufacturer: CVS Pharmacy
Category: otc | Type: HUMAN OTC DRUG LABEL
Date: 20251030

ACTIVE INGREDIENTS: MENTHOL 50 mg/1 1
INACTIVE INGREDIENTS: GLYCERIN; KAOLIN; ALCOHOL; DIHYDROXYALUMINUM AMINOACETATE ANHYDROUS; METHYLPARABEN; POLYSORBATE 80; WATER; TARTARIC ACID; TITANIUM DIOXIDE; PROPYLPARABEN; SODIUM POLYACRYLATE (8000 MW); SORBITAN MONOOLEATE

CVS Cold & Hot Medicated Patch Large and XL, 5ct 46821A ZDP

Active ingredient Purpose

Menthol 5%.................................................Topical analgesic

Uses

- temporarily relieves minor aches and pains of muscles and joints associated with:
- simple backache
- arthritis
- strains
- bruises
- sprains

Warnings

For external use only

Do not use

- on wounds or damaged skin
- with a heating pad
- on a children under 12 years of age with arthritis-like conditions

Ask a doctor before use if you have

- redness over the affected area

When using this product

- use only as directed
- avoid contact with eyes or mucous membranes
- do not bandage tightly
- discontinue use at least 1 hour before a bath or shower
- do not use immediately after a bath or shower

PREGNANCY OR BREAST FEEDING

If pregnant or breast-feeding, ask a health professional before use

Keep out of reach of children. If swallowed, get medical help or contact a Poison Control Center (1-800-222-1222) right away.

Directions

- open pouch and remove patch
- carefully peel off protective backing and apply sticky side to affected area
- adults and children 12 years of age and older:
- do not wear patch for more than 8 hours
- apply to affected area no more than 3 times daily
- children under 12 years of age: consult a doctor

Other information

- store at room temperature 20-25°C (68-77°F)

Inactive ingredients

alcohol, aluminum glycinate, glycerin, kaolin, methylparaben, polysorbate 80, propylparaben, purified water, sodium polyacrylate, sorbitan monooleate, tartaric acid, titanium dioxide

DOSAGE AND ADMINISTRATION

Distributed by: CVS Pharmacy, Inc.

One CVS Drive

Woonsocket, RI 02895

Made in China